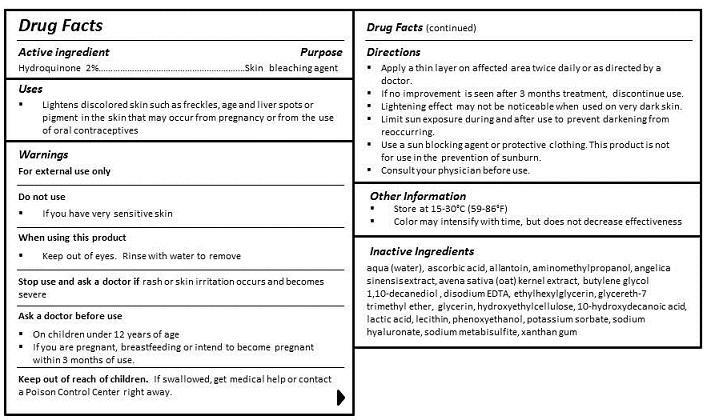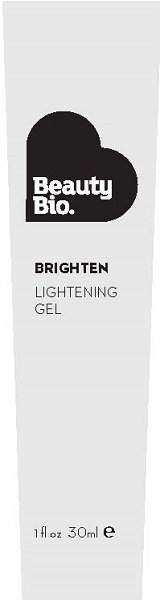 DRUG LABEL: BRIGHTEN
NDC: 54272-301 | Form: GEL
Manufacturer: CEN BEAUTY LLC
Category: otc | Type: HUMAN OTC DRUG LABEL
Date: 20130305

ACTIVE INGREDIENTS: HYDROQUINONE 2 g/100 mL
INACTIVE INGREDIENTS: WATER; ASCORBIC ACID; ALLANTOIN; AMINOMETHYLPROPANOL; GLYCERIN; OAT; ANGELICA SINENSIS WHOLE; BUTYLENE GLYCOL; 10-HYDROXYDECANOIC ACID; 1,10-DECANEDIOL; LECITHIN, SOYBEAN; EDETATE DISODIUM; LACTIC ACID; GLYCERETH-7 TRIMETHYL ETHER; ETHYLHEXYLGLYCERIN; HYDROXYETHYL CELLULOSE (100 MPA.S AT 2%); HYALURONATE SODIUM; SODIUM METABISULFITE; POTASSIUM SORBATE; XANTHAN GUM; PHENOXYETHANOL

ACTIVE INGREDIENT

ZINC OXIDE 15%

OCTINOXATE 6%

PURPOSE

SUNSCREEN

USES

- Lightens discolored skin such as freckles, age and liver spots or pigment in the skin that may occur from pregnancy or from the use of oral contraceptives

WARNINGS

FOR EXTERNAL USE ONLY

DO NOT USE

- IF YOU HAVE VERY SENSITIVE SKIN

WHEN USING THIS PRODUCT

- Keep out of eyes. Rinse with water to remove.

STOP USE AND ASK A DOCTOR IF RASH OCCURS.

KEEP OUT OF REACH OF CHILDREN. IF SWALLOWED, GET MEDICAL HELP OR CONTACT A POISON CONTROL CENTER RIGHT AWAY.

ASK A DOCTOR BEFORE USE

- On children under 12 years of age
- If you are pregnant, breastfeeding or intend to become pregnant within 3 months of use.

DIRECTIONS

- Apply a thin layer on affected area twice daily or as directed by a doctor.
- If no improvement is seen after 3 months treatment, discontinue use.
- Lightening effect may not be noticeable when used on very dark skin.
- Limit sun exposure during and after use to prevent darkening from reoccurring.
- Use a sun blocking agent or protective clothing. This product is not for use in the prevention of sunburn.
- Consult your physician before use.

Other Information

- STORE AT 15-30°C (59-86°F)
- PROTECT THIS PRODUCT FROM EXCESSIVE HEAT AND DIRECT SUN.

INACTIVE INGREDIENT

INGREDIENTS

aqua (water), cyclopentasiloxane, PEG-10 dimethicone, dimethicone, butylene glycol, cyclohexasiloxane, glycerin, carollina officinalis extract, algae extract, avena sativa (oat) kernel extract, angelica sinensis extract, 10-hydroxydecanoic acid, sebacic acid, 1,10-decanediol acid, betaine, dimethicone/vinyl dimethicone crosspolymer, lauryl PEG-9 polydimethylsiloxyethyl dimethicone, lecithin, dimethicone/PEG-10/15 crosspolymer, triethoxycaprylylsilane, decamethylcyclopentasiloxane, trifluoromethyl C1-C4 alkyl dimethicone, quaternium-90, bentonite, butylene glycol, sodium chloride, sodium citrate, ethylhexylglycerin, propylene carbonate, propylene glycol, potassium sorbate, methylisothiazolinone, iodopropynyl butylcarbamate, phenoxyethanol